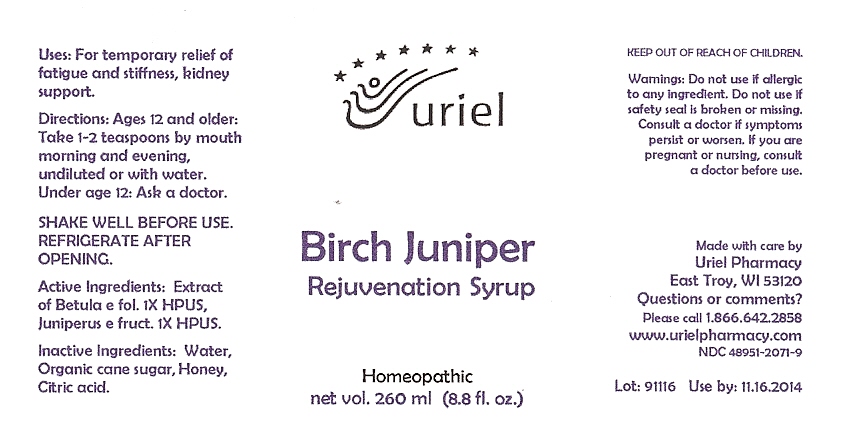 DRUG LABEL: Birch Juniper Rejuvenation
NDC: 48951-2071 | Form: SYRUP
Manufacturer: Uriel Pharmacy Inc
Category: homeopathic | Type: HUMAN OTC DRUG LABEL
Date: 20100201

ACTIVE INGREDIENTS: BETULA PENDULA LEAF 1 [hp_X]/1 1; JUNIPERUS COMMUNIS FRUIT 1 [hp_X]/1 1
INACTIVE INGREDIENTS: WATER; SUCROSE; HONEY; CITRIC ACID MONOHYDRATE

Birch Juniper Rejuvenation Syrup - 8.8 oz.

Purpose

Uses: For temporary relief of fatigue and stiffness, kidney support.

Dosage & Administration

Directions: Ages 12 and older: Take 1-2 teaspoons by mouth morning and evening, undiluted or with water. Under age 12: Ask a doctor.

SHAKE WELL BEFORE USE. REFRIGERATE AFTER OPENING.

OTC-Active Ingredient

Active Ingredients: Extract of Betula e fol. 1X HPUS, Juniperus e fruct. 1X HPUS.

Inactive Ingredient

Inactive Ingredients: Water, Organic cane sugar, Honey, Citric acid.

Keep out of reach of children

Do not use section

Warnings:Do not use if allergic to any ingredient. Do not use if safety seal is broken or missing.

Ask doctor section

Consult a doctor if symptoms persist or worsen.

Pregnancy or breast feeding section

If you are pregnant or nursing, consult a doctor before use.

Questions section

Made with care by
Uriel Pharmacy
East Troy, WI 53120
Questions or comments?
Please call 1.866.642.2858
www.urielpharmacy.com
NDC 48951-2071-9

Principal Display Panel

Birch Juniper

Rejuvenation Syrup

Homeopathic

net vol. 260 ml (8.8 fl. oz.)